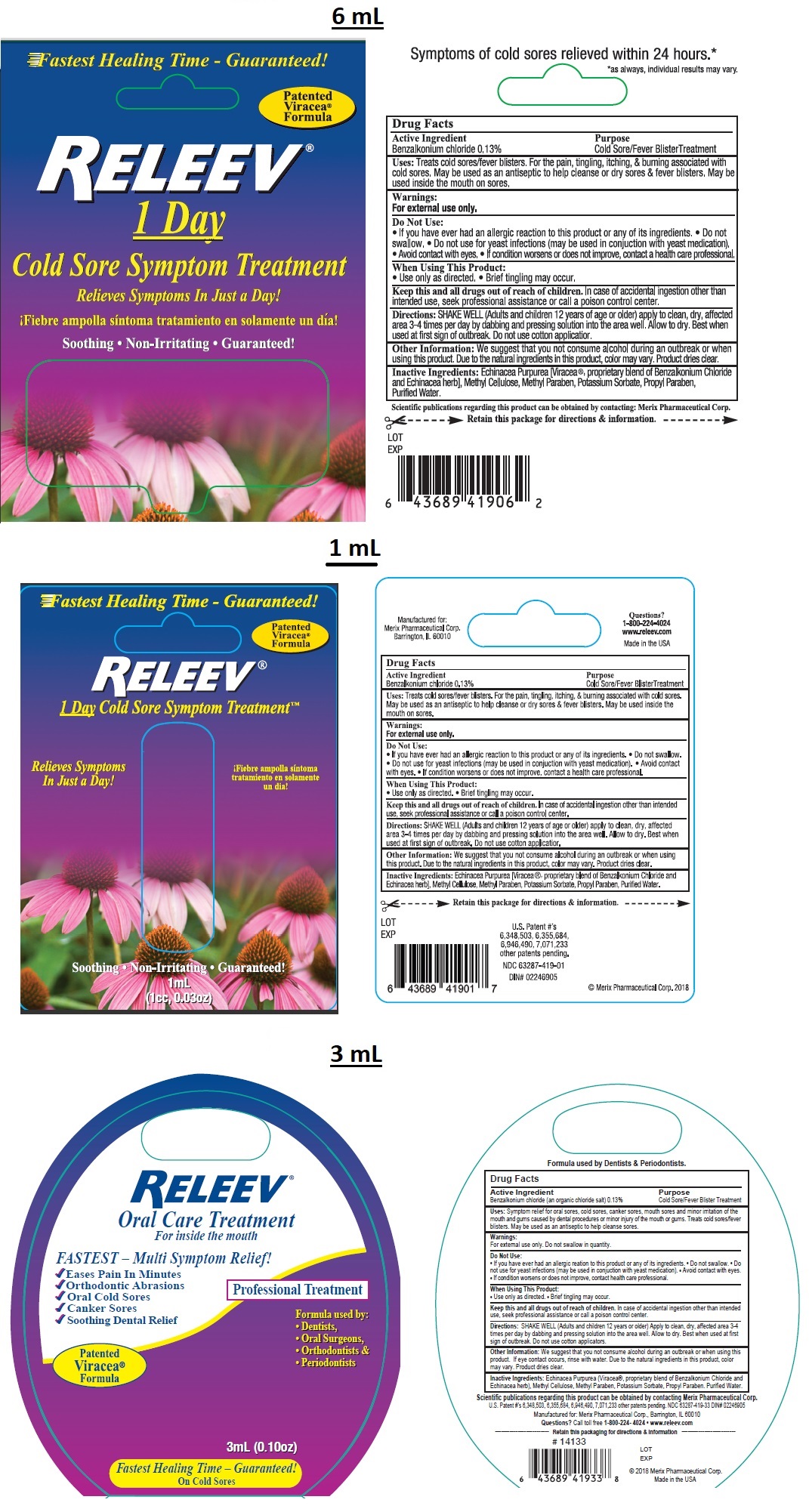 DRUG LABEL: RELEEV Cold Sore Treatment
NDC: 63287-419 | Form: LIQUID
Manufacturer: Merix Pharmaceutical Corp.
Category: otc | Type: HUMAN OTC DRUG LABEL
Date: 20220715

ACTIVE INGREDIENTS: BENZALKONIUM CHLORIDE 1.3 mg/1 mL
INACTIVE INGREDIENTS: HYPROMELLOSE 2910 (4000 MPA.S); ECHINACEA PURPUREA FLOWERING TOP; METHYLPARABEN; POTASSIUM SORBATE; WATER; PROPYLPARABEN

RELEEV 1 day Cold sore Symptom Treatment

Active ingredient

Benzalkonium chloride 0.13%

Purpose

Cold Sore/ Fever Blister Treatment

Uses:

Treats cold sores/ fever blisters. For the pain, tingling, itching, & burning associated with cold sores. May be used as an antiseptic to help cleanse or dry cold sores & fever blisters. May be used inside the mouth on sores.

Warnings:

For external use only

Do Not Use:

• If you have ever had an allergic reaction to this product or any of its ingredients. • Do not swallow. • Do not use for yeast infections (may be used in conjunction with yeast medication). • Avoid contact with eyes. • If condition worsens or does not improve, contact a health care professional.

When Using This Product

• Use only as directed • Brief tingling may occur.

KEEP OUT OF REACH OF CHILDREN

Keep this and all drugs out of reach of children. In case of accidental ingestion other than intended use, seek professional assistance or call a poison control center.

Directions:

SHAKE WELL (Adults and children 12 years of age or older) apply to clean, dry, affected area 3-4 times per day by dabbing and pressing solution into the area well. Allow to dry. Best when used at first sign of outbreak. Do not use cotton applicator.

Inactive Ingredients:

Echinacea Purpurea [Viracea®, proprietary blend of Benzalkonium Chloride and Echinacea herb], Methyl Cellulose, Methyl Paraben, Potassium Sorbate, Propyl Paraben, Purified Water,

Other Information:

We suggest that you not consume alcohol during an outbreak or when using this product. Due to the natural ingredients in this product, colour may vary. Product dries clear.